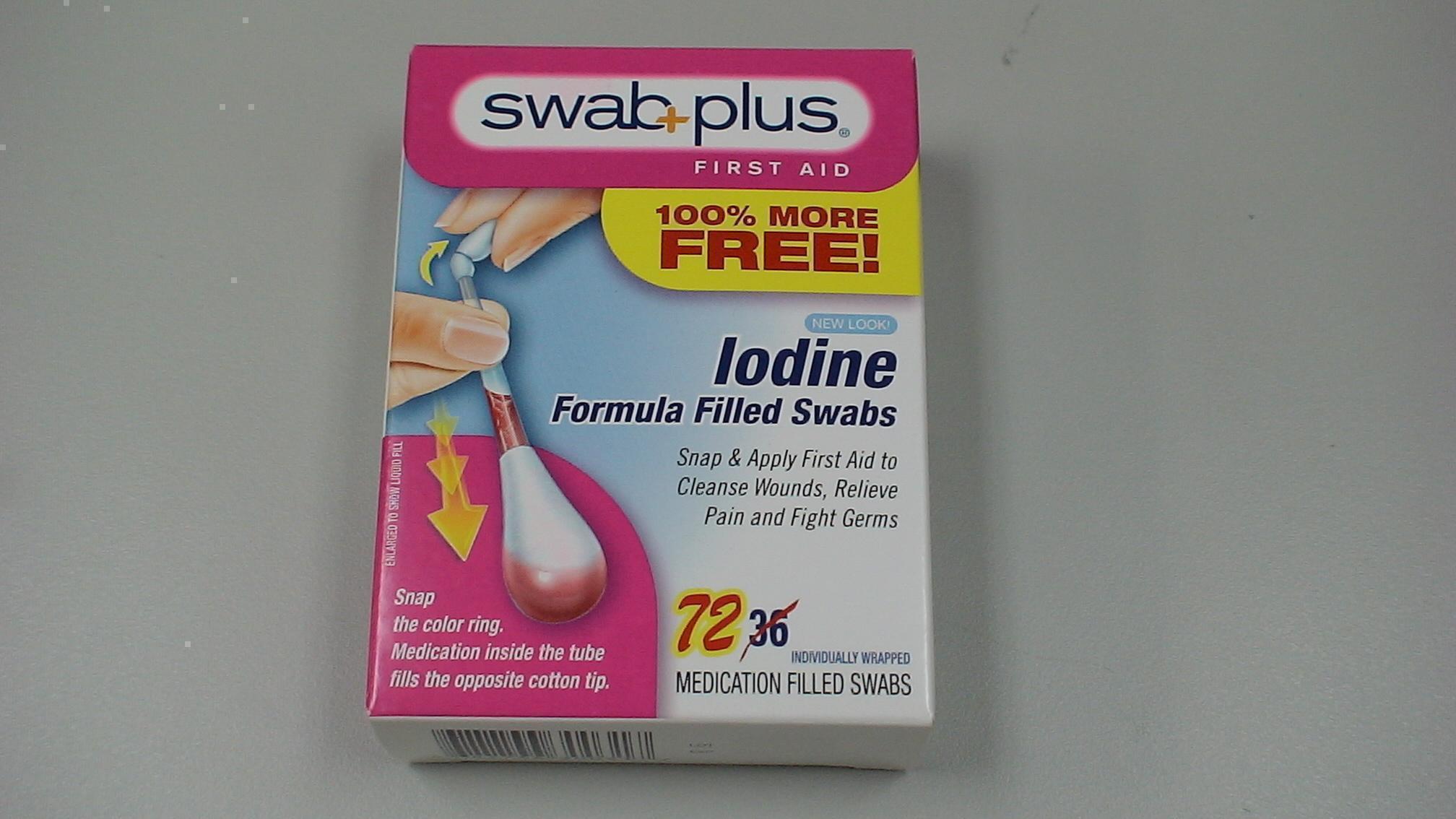 DRUG LABEL: Iodine
NDC: 65734-317 | Form: SOLUTION
Manufacturer: Swabplus Inc.
Category: otc | Type: HUMAN OTC DRUG LABEL
Date: 20150216

ACTIVE INGREDIENTS: Povidone-Iodine 10 mg/1 mL
INACTIVE INGREDIENTS: Water; Glycerin; Sodium Hydroxide

Idoine Formula Filled Swab

Drug Facts Active ingredient

Povidone Iodine 10%, equal to 1% available Iodine

Purpose

Antiseptic

Uses

First aid to help prevent infection due to minor cuts, scrapes and burns.

Keep out of reach of children

if swallowed, get medical help of contact a Poison Control Center right away.

Directions

- Hold the swab vertically, with the color ring tip upwards. Hold in the center of the tube with one hand at the color ring with the other.
- Gently snap the tip with the color ring. Formula inside the tube flows down and fills the opposite tip.
- Apply the product to the affected area.
- Discard swab after use.

Warnings

For external use only. Keep out of eyes and ear canal. Non-Sterile. Discontinue use if irritation occurs.

Do not use. if you are sensitive to Iodine. longer than one week unless directed by a doctor.

Stop use and ask a doctor if. you have deep or puncture wounds, or serious burns. redness, irritation, swelling or pain continues or increases. infection occurs

Administration

For adulta and children 2 and older: for minor wounds, burns and infections, apply directly to affected area. May be covered with bandage.

Children under 2 years of ages: Do not use, consult a doctor.

Other information: Store at room temperature. Avoid direct sunlight, excessive heat and moisture.

Inactive ingredients

Glycerin, water

Manufacturer Statements

Patented and manufactured by Swabplus Inc. Rancho Cucamonga, CA 91730 USA Made in USA

The COLOR RING is copyrighted by Swabplus Inc.©2007 SWABPLUS INC.

Package and Labeling

Image of iodine carton